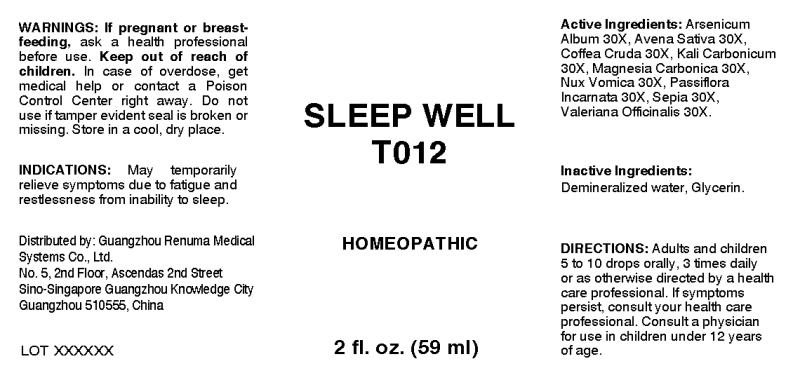 DRUG LABEL: Sleep Well
NDC: 71742-0006 | Form: LIQUID
Manufacturer: Guangzhou Renuma Medical Systems Co., Ltd
Category: homeopathic | Type: HUMAN OTC DRUG LABEL
Date: 20171024

ACTIVE INGREDIENTS: ARSENIC TRIOXIDE 30 [hp_X]/1 mL; AVENA SATIVA FLOWERING TOP 30 [hp_X]/1 mL; ARABICA COFFEE BEAN 30 [hp_X]/1 mL; POTASSIUM CARBONATE 30 [hp_X]/1 mL; MAGNESIUM CARBONATE 30 [hp_X]/1 mL; STRYCHNOS NUX-VOMICA SEED 30 [hp_X]/1 mL; PASSIFLORA INCARNATA FLOWERING TOP 30 [hp_X]/1 mL; SEPIA OFFICINALIS JUICE 30 [hp_X]/1 mL; VALERIAN 30 [hp_X]/1 mL
INACTIVE INGREDIENTS: WATER; GLYCERIN

Drug Facts:

ACTIVE INGREDIENTS:

Arsenicum Album 30X, Avena Sativa 30X, Coffea Cruda 30X, Kali Carbonicum 30X, Magnesia Carbonica 30X, Nux Vomica 30X, Passiflora Incarnata 30X, Sepia 30X, Valeriana Officinalis 30X.

INDICATIONS:

May temporarily relieve symptoms due to fatigue and restlessness from inability to sleep.

WARNINGS:

If pregnant or breast-feeding, ask a health care professional before use.

Keep out of reach of children. In case of overdose, get medical help or contact a Poison Control Center right away.

Do not use if tamper evident seal is broken or missing.

Store in cool, dry place.

Keep out of reach of children. In case of overdose, get medical help or contact a Poison Control Center right away.

DIRECTIONS:

Adults and children 5 to 10 drops orally, 3 times daily or as otherwise directed by a health care professional. If symptoms persist, consult your health care professional. Consult a physician for use in children under 12 years of age.

INDICATIONS:

May temporarily relieve symptoms due to fatigue and restlessness from inability to sleep.

INACTIVE INGREDIENTS:

Demineralized water, Glycerin

QUESTIONS:

Distributed by:
Guangzhou Renuma Medical
Systems Co., Ltd.
No. 5, 2nd Floor, Ascendas 2nd Street
Sino-Singapore Guangzhou Knowledge City
Guangzhou 510555, China

PACKAGE LABEL DISPLAY:

SLEEP WELL
T012
HOMEOPATHIC
2 fl. oz. (59 ml)